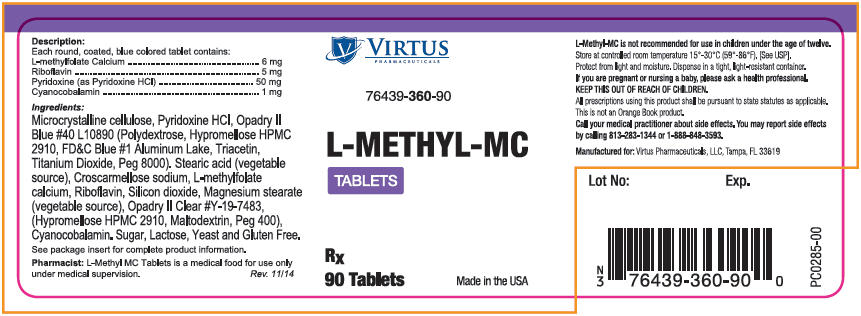 DRUG LABEL: L-Methyl-MC
NDC: 76439-360 | Form: TABLET, COATED
Manufacturer: Virtus Pharmaceuticals
Category: other | Type: MEDICAL FOOD
Date: 20150917

ACTIVE INGREDIENTS: Levomefolate Calcium 6 mg/1 1; Riboflavin 5 mg/1 1; Pyridoxine Hydrochloride 50 mg/1 1; Cyanocobalamin 1 mg/1 1
INACTIVE INGREDIENTS: Cellulose, Microcrystalline; Polydextrose; FD&C Blue No. 1; Aluminum Oxide; Triacetin; Titanium Dioxide; Polyethylene Glycol 8000; Stearic Acid; Croscarmellose Sodium; Silicon Dioxide; Magnesium Stearate; Maltodextrin; Polyethylene Glycol 400

L-Methyl-MC Tablets

A medical food for the dietary management of hyperhomocysteinemia.

Description

Each round coated blue colored tablet contains:

Dietary Ingredients:
L-methylfolate Calcium | 6 mg
Riboflavin | 5 mg
Pyridoxine (as Pyridoxine HCl) | 50 mg
Cyanocobalamin | 1 mg

Ingredients

Microcrystalline Cellulose, Pyridoxine HCl,Opadry II Blue #40L10890 (Polydextrose, Hypromellose HPMC 2910, FD&C Blue #1 Aluminum Lake, Triacetin, Titanium Dioxide, Peg 8000). Stearic Acid (Vegetable Source), Croscarmellose Sodium, L-methylfolate Calcium, Riboflavin, Silicon Dioxide, Magnesium Stearate (Vegetable Source), Opadry II Clear #Y-19-7483, (Hypromellose HPMC 2910, Maltodextrin, Peg 400), Cyanocobalamin.

L-Methyl-MC Tablets do not contain sugar, lactose, yeast or gluten.

Indication and Usage

L-Methyl-MC Tablets are indicated for the distinct nutritional requirements of individuals under medical supervision for hyperhomocysteinemia; with particular emphasis for individuals diagnosed with or at risk for mild to moderate: cognitive impairment^1, vascular dementia^2, or Alzheimer's disease^3.

Precautions

Folates, when administered as a single agent in doses above 0.1mg daily, may obscure pernicious anemia in that hematologic remission can occur while neurological manifestations remain progressive. The 1 mg of cyanocobalamin contained in L-Methyl-MC Tablets has been shown to provide an adequate amount of cyanocobalamin to address this precaution^4. A safe upper limit of 100 mg per day has been established for the unsupervised medical use of pyridoxine. Consider all sources of pyridoxine supplementation when prescribing L-Methyl-MC Tablets.

Adverse Reactions

While allergic sensitization has been reported following both oral and parenteral administration of folic acid, allergic sensitization has not been reported with the use of L-Methylfolate Calcium. Paresthesia, somnolence, nausea and headaches have been reported with pyridoxine. Mild transient diarrhea, polycythemia vera, itching, transitory exanthema and the feeling of swelling of the entire body has been associated with cyanocobalamin. Transient headaches have been reported infrequently with the use of L-Methyl-MC Tablets. If headaches should occur with the use of L-Methyl-MC Tablets consult with your medical practitioner.

Contraindications

Known hypersensitivity to any of the components in the product is a contraindication.

Drug Interactions

L-Methyl-MC Tablets added to other drugs

High dose folic acid may result in decreased serum levels for pyrimethamine and first-generation anticonvulsants (carbamazepine, fosphenytoin, phenytoin, phenobarbital, primidone, valproic acid, valproate). This may possibly reduce first generation anticonvulsants effectiveness and/or increasing the frequency of seizures in susceptible patients. While the concurrent use of folic acid and first generation anticonvulsants or pyrimethamine may result in decreased efficacy of anticonvulsants, no such decreased effectiveness has been reported with the use of L-methylfolate. Nevertheless, caution should be used when prescribing L-METHYL-MC TABLETS among patients who are receiving treatment with first generation anticonvulsants or pyrimethamine. Pyridoxine should not be given to patients receiving the drug levodopa, because the action of levodopa is antagonized by pyridoxine. However, pyridoxine may be used concurrently in patients receiving a preparation containing both carbidopa and levodopa. Capecitabine (Xeloda®) toxicity may increase with the addition of leucovorin (5-formyltetrahydrofolate) (folate).

Drugs added to L-METHYL-MC TABLETS

Antibiotics may alter the intestinal microflora and may decrease the absorption of cyanocobalamin. Cholestyramine, colchicines or colestipol may decrease the enterohepatic reabsorption of cyanocobalamin. Metformin, para-aminosalicylic acid and potassium chloride may decrease the absorption of cyanocobalamin. Nitrous oxide can produce a functional cyanocobalamin deficiency. Several drugs are associated with lowering serum folate levels or reducing the amount of active folate available. First generation anticonvulsants (carbamazepine, fosphenytoin, phenytoin, phenobarbital, primidone, valproic acid, valproate) and lamotrigine (a second-generation anticonvulsant) may decrease folate plasma levels. Information on other second-generation anticonvulsants impact on folate levels is limited and cannot be ruled out. Methotrexate, alcohol (in excess), sulfasalazine, cholestyramine, colchicine, colestipol, L-dopa, methylprednisone, NSAIDs (high dose), pancreatic enzymes (pancrelipase, pancratin), pentamidine, pyrimethamine, smoking, triamterene, and trimethoprim may decrease folate plasma levels. Warfarin can produce significant impairment in folate status after a 6 month therapy.

Patient Information

L-Methyl-MC Tablets is a medical food for use only under medical supervision.

Dosage and Administration

Usual adult dose is one to two tablets daily or as directed by your medical practitioner. L-Methyl-MC Tablets is not recommended for use with children under the age of twelve.

How Supplied

Available as a round coated blue colored tablet. Debossed with "V360" on one side and blank on the other. Commercial product is supplied in bottles of 90 tablets (76439-360-90 [Virtus Pharmaceuticals, LLC does not represent this product code to be a National Drug Code (NDC) number. Instead, Virtus Pharmaceuticals, LLC has assigned a product code formatted according to standard industry practice to meet the formatting requirements of pharmacy and health insurance computer systems.]). Use under medical/physician supervision.

Storage

Store at controlled room temperature 15ºC to 30ºC (59ºF to 86ºF) (See USP).

Patents

Some or all of the following-patents may apply:

U.S. Patent No. 5,563,126
U.S. Patent No. 5,795,873
U.S. Patent No. 5,997,915
U.S. Patent No. 6,011,040
U.S. Patent No. 6,207,651
U.S. Patent No. 6,254,904
U.S. Patent No. 6,297,224
U.S. Patent No. 6,528,496
and other pending patent applications.

References

^1 Lehmann M, Regland B, Blennow K, and Gottfries CG: Vitamin B12-B6-Folate Treatment Improves Blood-Brain Barrier Function in Patients with Hyperhomocysteinaemia and Mild Cognitive Impairment. Dementia and Geriatric Cognitive Disorders 2003;16:145-150.

^2 Nilsson K, Gustafson L, and Hultberg B: Improvement of cognitive functions after cobalamin/folate supplementation in elderly patients with dementia and elevated plasma homocysteine. International Journal of Geriatric Psychiatry 2001;16:609-614.

^3 Seshadri S, Beiser A, Selhub J, Jacques PF, Rosenberg IH, D'Agostino RB, Wilson PWF, and Wolf PA: Plasma Homocysteine As A Risk Factor For Dementia And Alzheimer's Disease. New England Journal of Medicine 2002:Vol346, No. 7:476-483.

^4 Lederle FA: Oral cobalamin for pernicious anaemia: medicine's best kept secret. JAMA 1991;265:94-95.

Manufactured for:
Virtus Pharmaceuticals, LLC
Tampa, FL 33619

PC0296-00
Revised 11/14

PRINCIPAL DISPLAY PANEL - 90 Tablet Bottle Label

VIRTUS
PHARMACEUTICALS

76439-360-90

L-METHYL-MC

TABLETS

RX
90 Tablets
Made in the USA